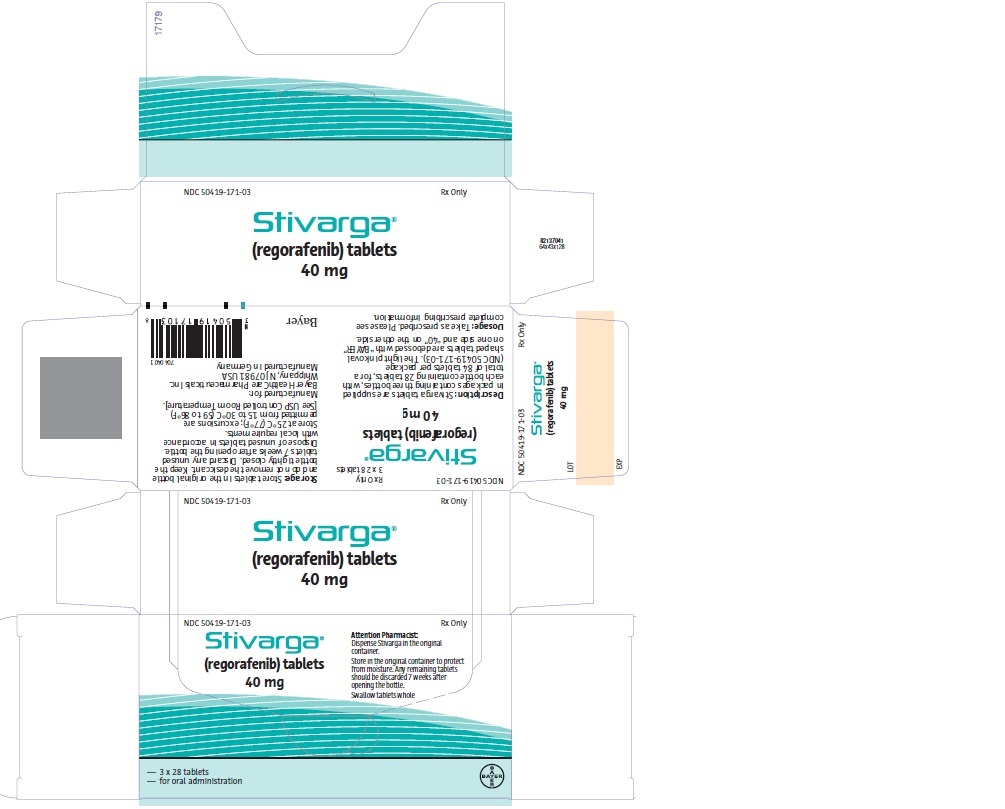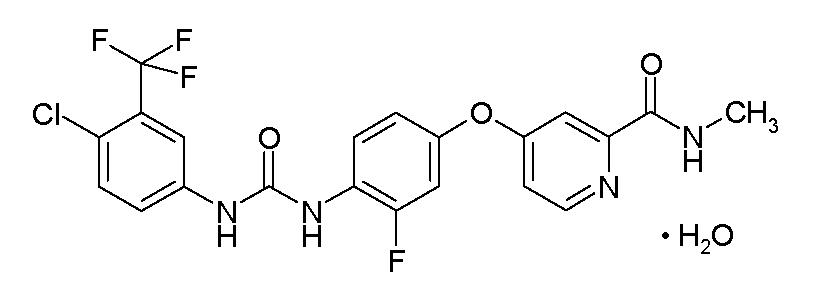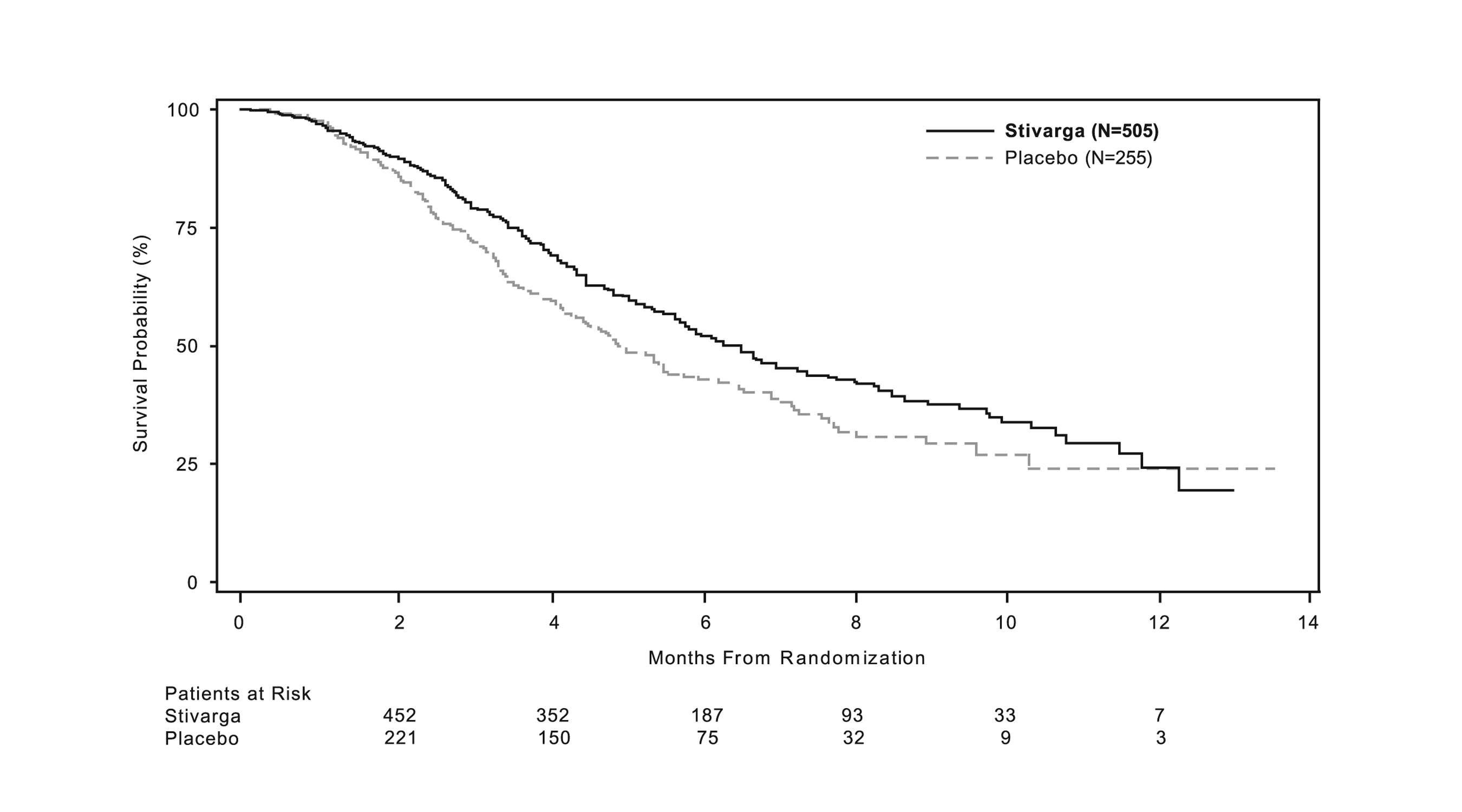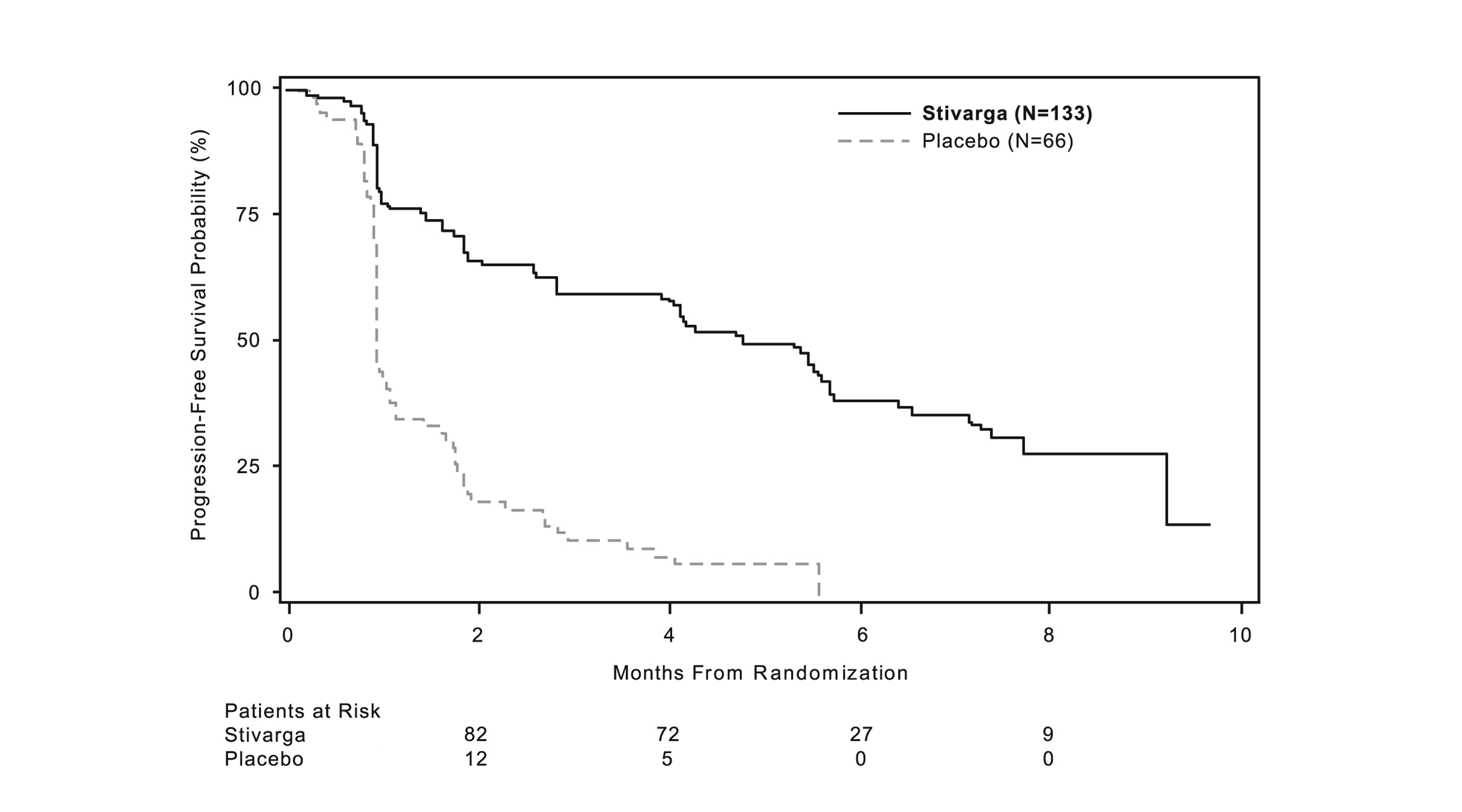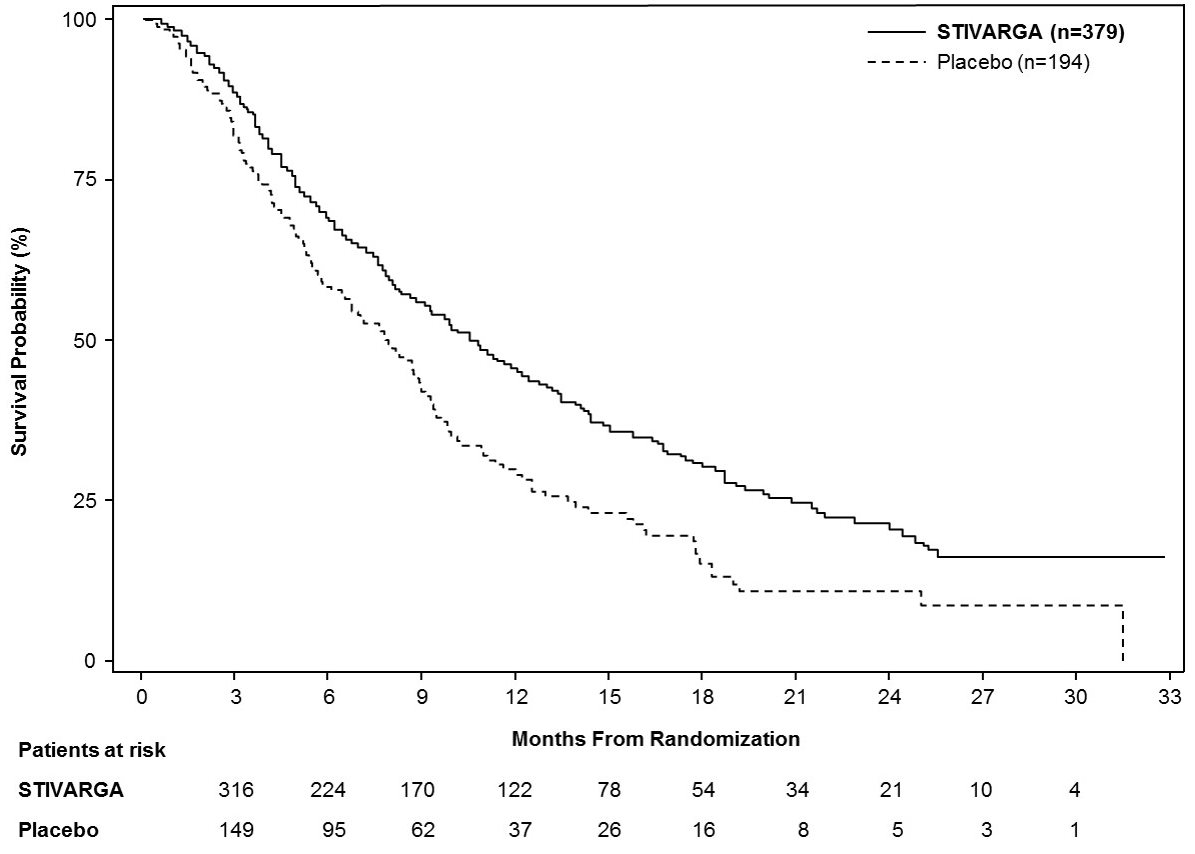 DRUG LABEL: Stivarga
NDC: 50419-171 | Form: TABLET, FILM COATED
Manufacturer: Bayer HealthCare Pharmaceuticals Inc.
Category: prescription | Type: HUMAN PRESCRIPTION DRUG LABEL
Date: 20260209

ACTIVE INGREDIENTS: REGORAFENIB 40 mg/1 1
INACTIVE INGREDIENTS: MICROCRYSTALLINE CELLULOSE; CROSCARMELLOSE SODIUM; MAGNESIUM STEARATE; SILICON DIOXIDE; FERRIC OXIDE RED; FERRIC OXIDE YELLOW; SOYBEAN LECITHIN; POLYETHYLENE GLYCOL 3350; POLYVINYL ALCOHOL, UNSPECIFIED; TALC; TITANIUM DIOXIDE; POVIDONE, UNSPECIFIED

HIGHLIGHTS OF PRESCRIBING INFORMATION

These highlights do not include all the information needed to use STIVARGA safely and effectively. See full prescribing information for STIVARGA.
STIVARGA® (regorafenib) tablets, for oral use
Initial U.S. Approval: 2012

WARNING: HEPATOTOXICITY

See full prescribing information for complete boxed warning.

- Severe and sometimes fatal hepatotoxicity has occurred in clinical trials. (5.1)
- Monitor hepatic function prior to and during treatment. (5.1)
- Interrupt and then reduce or discontinue STIVARGA for hepatotoxicity as manifested by elevated liver function tests or hepatocellular necrosis, depending upon severity and persistence. (2.2)

RECENT MAJOR CHANGES

Warnings and Precautions (5.1) | 2/2026

1 INDICATIONS AND USAGE

STIVARGA is a kinase inhibitor indicated for the treatment of adult patients with:

- Metastatic colorectal cancer (CRC) who have been previously treated with fluoropyrimidine-, oxaliplatin- and irinotecan-based chemotherapy, an anti-VEGF therapy, and, if RAS wild-type, an anti-EGFR therapy. (1.1)
- Locally advanced, unresectable or metastatic gastrointestinal stromal tumor (GIST) who have been previously treated with imatinib mesylate and sunitinib malate. (1.2)
- Hepatocellular carcinoma (HCC) who have been previously treated with sorafenib (1.3)

2 DOSAGE AND ADMINISTRATION

- Recommended dose: 160 mg orally, once daily for the first 21 days of each 28-day cycle. (2.1)
- Take STIVARGA after a low-fat meal. (2.1, 12.3)

3 DOSAGE FORMS AND STRENGTHS

Tablets: 40 mg (3)

4 CONTRAINDICATIONS

None.

5 WARNINGS AND PRECAUTIONS

- Hepatotoxicity: Monitor liver function tests. Withhold and then reduce or discontinue STIVARGA based on severity and duration. (5.1)
- Infections: Withhold STIVARGA in patients with worsening or severe infections. (5.2)
- Hemorrhage: Permanently discontinue STIVARGA for severe or life-threatening hemorrhage. (5.3)
- Gastrointestinal perforation or fistula: Discontinue STIVARGA. (5.4)
- Dermatologic toxicity: Withhold and then reduce or discontinue STIVARGA depending on severity and persistence of dermatologic toxicity. (5.5)
- Hypertension: Temporarily or permanently withhold STIVARGA for severe or uncontrolled hypertension. (5.6)
- Cardiac ischemia and infarction: Withhold STIVARGA for new or acute cardiac ischemia/infarction and resume only after resolution of acute ischemic events. (5.7)
- Reversible posterior leukoencephalopathy syndrome (RPLS): Discontinue STIVARGA. (5.8)
- Risk of impaired wound healing: Withhold for at least 2 weeks prior to elective surgery. Do not administer for at least 2 weeks after major surgery and until adequate wound healing. The safety of resumption of STIVARGA after resolution of wound healing complications has not been established. (5.9)
- Embryo-fetal toxicity: Can cause fetal harm. Advise women of potential risk to a fetus and to use effective contraception during treatment and for 2 months after the final dose. Advise males to use effective contraception for 2 months after the final dose. (5.10, 8.1, 8.3)

6 ADVERSE REACTIONS

The most common adverse reactions (≥20%) are pain (including gastrointestinal and abdominal pain), HFSR, asthenia/fatigue, diarrhea, decreased appetite/food intake, hypertension, infection, dysphonia, hyperbilirubinemia, fever, mucositis, weight loss, rash, and nausea. (6)

To report SUSPECTED ADVERSE REACTIONS, contact Bayer HealthCare Pharmaceuticals Inc. at 1-888-842-2937 or FDA at 1-800-FDA-1088 or www.fda.gov/medwatch

7 DRUG INTERACTIONS

- Strong CYP3A4 inducers: Avoid strong CYP3A4 inducers. (7.1)
- Strong CYP3A4 inhibitors: Avoid strong CYP3A4 inhibitors. (7.2)
- BCRP substrates: Monitor patients closely for symptoms of increased exposure to BCRP substrates. (7.3)

8 USE IN SPECIFIC POPULATIONS

Nursing Mothers: Discontinue drug or nursing, taking into consideration the importance of the drug to the mother. (8.3)

FULL PRESCRIBING INFORMATION

WARNING: HEPATOTOXICITY

- Severe and sometimes fatal hepatotoxicity has occurred in clinical trials [see Warnings and Precautions (5.1)].
- Monitor hepatic function prior to and during treatment [see Warnings and Precautions (5.1)].
- Interrupt and then reduce or discontinue STIVARGA for hepatotoxicity as manifested by elevated liver function tests or hepatocellular necrosis, depending upon severity and persistence [see Dosage and Administration (2.2)].

1 INDICATIONS AND USAGE

1.1 Colorectal Cancer

STIVARGA is indicated for the treatment of adult patients with metastatic colorectal cancer (CRC) who have been previously treated with fluoropyrimidine-, oxaliplatin- and irinotecan-based chemotherapy, an anti-VEGF therapy, and, if RAS wild-type, an anti-EGFR therapy.

1.2 Gastrointestinal Stromal Tumors

STIVARGA is indicated for the treatment of adult patients with locally advanced, unresectable or metastatic gastrointestinal stromal tumor (GIST) who have been previously treated with imatinib mesylate and sunitinib malate.

1.3 Hepatocellular Carcinoma

STIVARGA is indicated for the treatment of adult patients with hepatocellular carcinoma (HCC) who have been previously treated with sorafenib.

2 DOSAGE AND ADMINISTRATION

2.1 Recommended Dose

The recommended dose is 160 mg STIVARGA (four 40 mg tablets) taken orally once daily for the first 21 days of each 28-day cycle. Continue treatment until disease progression or unacceptable toxicity.

Take STIVARGA at the same time each day. Swallow tablet whole with water after a low-fat meal that contains less than 600 calories and less than 30% fat [see Clinical Pharmacology (12.3)]. Do not take two doses of STIVARGA on the same day to make up for a missed dose from the previous day.

2.2 Dose Modifications

If dose modifications are required, reduce the dose in 40 mg (one tablet) increments; the lowest recommended daily dose of STIVARGA is 80 mg daily.

Interrupt STIVARGA for the following:

- Grade 2 hand-foot skin reaction (HFSR) [palmar-plantar erythrodysesthesia syndrome (PPES)] that is recurrent or does not improve within 7 days despite dose reduction; interrupt therapy for a minimum of 7 days for Grade 3 HFSR
- Symptomatic Grade 2 hypertension
- Any Grade 3 or 4 adverse reaction
- Worsening infection of any grade

Reduce the dose of STIVARGA to 120 mg:

- For the first occurrence of Grade 2 HFSR of any duration
- After recovery of any Grade 3 or 4 adverse reaction except infection
- For Grade 3 aspartate aminotransferase (AST)/alanine aminotransferase (ALT) elevation, only resume if the potential benefit outweighs the risk of hepatotoxicity

Reduce the dose of STIVARGA to 80 mg:

- For re-occurrence of Grade 2 HFSR at the 120 mg dose
- After recovery of any Grade 3 or 4 adverse reaction at the 120 mg dose (except hepatotoxicity or infection)

Discontinue STIVARGA permanently for the following:

- Failure to tolerate 80 mg dose
- Any occurrence of AST or ALT more than 20 times the upper limit of normal (ULN)
- Any occurrence of AST or ALT more than 3 times ULN with concurrent bilirubin more than 2 times ULN
- Re-occurrence of AST or ALT more than 5 times ULN despite dose reduction to 120 mg
- For any Grade 4 adverse reaction; only resume if the potential benefit outweighs the risks

3 DOSAGE FORMS AND STRENGTHS

STIVARGA is a 40 mg, light pink, oval-shaped, film-coated tablet, debossed with 'BAYER' on one side and '40' on the other side.

4 CONTRAINDICATIONS

None.

5 WARNINGS AND PRECAUTIONS

5.1 Hepatotoxicity

Severe drug-induced liver injury with fatal outcome occurred in STIVARGA-treated patients in clinical trials. In most cases, liver dysfunction occurred within the first 2 months of therapy and was characterized by a hepatocellular pattern of injury. Additionally, hyperammonemic encephalopathy, including fatal cases, have been reported in the postmarketing setting in patients treated with STIVARGA. The risk of hyperammonemic encephalopathy appears increased in patients with liver dysfunction, liver metastases, or primary liver cancer.

In the CORRECT study, fatal hepatic failure occurred in 1.6% of patients in the regorafenib arm and in 0.4% of patients in the placebo arm. In the GRID study, fatal hepatic failure occurred in 0.8% of patients in the regorafenib arm. In the RESORCE study, there was no increase in the incidence of fatal hepatic failure as compared to placebo [see Adverse Reactions (6.1)].

Obtain liver function tests (ALT, AST, and bilirubin) before initiation of STIVARGA and monitor at least every two weeks during the first 2 months of treatment. Thereafter, monitor monthly or more frequently as clinically indicated. Monitor liver function tests weekly in patients experiencing elevated liver function tests until improvement to less than 3 times the ULN or baseline. For patients who develop unexplained lethargy or changes in mental status, measure ammonia level and initiate appropriate clinical management.

Temporarily hold and then reduce or permanently discontinue STIVARGA depending on the severity and persistence of hepatotoxicity as manifested by elevated liver function tests or hepatocellular necrosis [see Dosage and Administration (2.2) and Use in Specific Populations (8.6)]. If hyperammonemic encephalopathy is confirmed, withhold and consider permanent discontinuation of STIVARGA.

5.2 Infections

STIVARGA caused an increased risk of infections. The overall incidence of infection (Grades 1-5) was higher (32% vs. 17%) in 1142 STIVARGA-treated patients as compared to the control arm in randomized placebo‑controlled trials.The incidence of grade 3 or greater infections in STIVARGA treated patients was 9%. The most common infections were urinary tract infections (5.7%), nasopharyngitis (4.0%), mucocutaneous and systemic fungal infections (3.3%) and pneumonia (2.6%). Fatal outcomes caused by infection occurred more often in patients treated with STIVARGA (1.0%) as compared to patients receiving placebo (0.3%); the most common fatal infections were respiratory (0.6% in STIVARGA-treated patients vs 0.2% in patients receiving placebo).

Withhold STIVARGA for Grade 3 or 4 infections, or worsening infection of any grade. Resume STIVARGA at the same dose following resolution of infection [see Dosage and Administration (2.2)].

5.3 Hemorrhage

STIVARGA caused an increased incidence of hemorrhage. The overall incidence (Grades 1-5) was 18.2% in 1142 patients treated with STIVARGA and 9.5% in patients receiving placebo in randomized, placebo‑controlled trials. The incidence of grade 3 or greater hemorrhage in patients treated with STIVARGA was 3.0%. The incidence of fatal hemorrhagic events was 0.7%, involving the central nervous system or the respiratory, gastrointestinal, or genitourinary tracts.

Permanently discontinue STIVARGA in patients with severe or life-threatening hemorrhage. Monitor INR levels more frequently in patients receiving warfarin [see Clinical Pharmacology (12.3)].

5.4 Gastrointestinal Perforation or Fistula

Gastrointestinal perforation occurred in 0.6% of 4518 patients treated with STIVARGA across all clinical trials of STIVARGA administered as a single agent; this included eight fatal events.

Gastrointestinal fistula occurred in 0.8% of patients treated with STIVARGA and 0.2% of patients in placebo arm across randomized, placebo-controlled trials. Permanently discontinue STIVARGA in patients who develop gastrointestinal perforation or fistula.

5.5 Dermatologic Toxicity

In randomized, placebo-controlled trials, adverse skin reactions occurred in 71.9% of patients in the regorafenib arm and in 25.5% of patients in the placebo arm, including hand-foot skin reaction (HFSR) also known as palmar-plantar erythrodysesthesia syndrome (PPES), and severe rash requiring dose modification.

In the randomized, placebo-controlled trials, the overall incidence of HFSR was higher in 1142 STIVARGA-treated patients (53%) than in the placebo-treated patients (8%). Most cases of HFSR in STIVARGA-treated patients appeared during the first cycle of treatment. The incidences of Grade 3 HFSR (16% versus <1%), Grade 3 rash (3% versus <1%), serious adverse reactions of erythema multiforme (<0.1% vs. 0%) and Stevens-Johnson Syndrome (<0.1% vs. 0%) were also higher in STIVARGA-treated patients [see Adverse Reactions (6.1)]. Across all trials, a higher incidence of HFSR was observed in Asian patients treated with STIVARGA (all grades: 72%; Grade 3: 18%) [see Use in Specific Populations (8.8)].

Toxic epidermal necrolysis occurred in 0.02% of 4518 STIVARGA-treated patients across all clinical trials of STIVARGA administered as a single agent.

Withhold STIVARGA, reduce the dose, or permanently discontinue STIVARGA depending on the severity and persistence of dermatologic toxicity [see Dosage and Administration (2.2)]. Institute supportive measures for symptomatic relief.

5.6 Hypertension

In randomized, placebo-controlled trials, hypertensive crisis occurred in 0.2% of patients in the regorafenib arms and in none of the patients in the placebo arms. STIVARGA caused an increased incidence of hypertension (30% versus 8% in CORRECT, 59% versus 27% in GRID, and 31% versus 6% in RESORCE) [see Adverse Reactions (6.1)]. The onset of hypertension occurred during the first cycle of treatment in most patients who developed hypertension (67% in randomized, placebo-controlled trials).

Do not initiate STIVARGA unless blood pressure is adequately controlled. Monitor blood pressure weekly for the first 6 weeks of treatment and then every cycle, or more frequently, as clinically indicated. Temporarily or permanently withhold STIVARGA for severe or uncontrolled hypertension [see Dosage and Administration (2.2)].

5.7 Cardiac Ischemia and Infarction

STIVARGA increased the incidence of myocardial ischemia and infarction (0.9% vs 0.2%) in randomized placebo-controlled trials [see Adverse Reactions (6.1)]. Withhold STIVARGA in patients who develop new or acute onset cardiac ischemia or infarction. Resume STIVARGA only after resolution of acute cardiac ischemic events, if the potential benefits outweigh the risks of further cardiac ischemia.

5.8 Reversible Posterior Leukoencephalopathy Syndrome

Reversible posterior leukoencephalopathy syndrome (RPLS), a syndrome of subcortical vasogenic edema diagnosed by characteristic finding on MRI, occurred in one of 4800 STIVARGA-treated patients across all clinical trials. Perform an evaluation for RPLS in any patient presenting with seizures, severe headache, visual disturbances, confusion or altered mental function. Discontinue STIVARGA in patients who develop RPLS.

5.9 Risk of Impaired Wound Healing

Impaired wound healing complications can occur in patients who receive drugs that inhibit the VEGF signaling pathway. Therefore, STIVARGA has the potential to adversely affect wound healing.

Withhold STIVARGA for at least 2 weeks prior to elective surgery. Do not administer for at least 2 weeks following major surgery and until adequate wound healing. The safety of resumption of STIVARGA after resolution of wound healing complications has not been established.

5.10 Embryo-Fetal Toxicity

Based on animal studies and its mechanism of action, STIVARGA can cause fetal harm when administered to a pregnant woman. There are no available data on STIVARGA use in pregnant women. Regorafenib was embryolethal and teratogenic in rats and rabbits at exposures lower than human exposures at the recommended dose, with increased incidences of cardiovascular, genitourinary, and skeletal malformations. Advise pregnant women of the potential risk to a fetus.

Advise females of reproductive potential to use effective contraception during treatment with STIVARGA and for 2 months after the final dose. Advise males with female partners of reproductive potential to use effective contraception during treatment with STIVARGA and for 2 months after the final dose [see Use in Specific Populations (8.1), (8.3)].

6 ADVERSE REACTIONS

The following serious adverse reactions are discussed elsewhere in the labeling:

- Hepatotoxicity [see Warnings and Precautions (5.1)]
- Infections [see Warnings and Precautions (5.2)]
- Hemorrhage [see Warnings and Precautions (5.3)]
- Gastrointestinal Perforation or Fistula [see Warnings and Precautions (5.4)]
- Dermatological Toxicity [see Warnings and Precautions (5.5)]
- Hypertension [see Warnings and Precautions (5.6)]
- Cardiac Ischemia and Infarction [see Warnings and Precautions (5.7)]
- Reversible Posterior Leukoencephalopathy Syndrome (RPLS) [see Warnings and Precautions (5.8)]

6.1 Clinical Trials Experience

Because clinical trials are conducted under widely varying conditions, adverse reaction rates observed in the clinical trials of a drug cannot be directly compared to rates in the clinical trials of another drug and may not reflect the rate observed in practice.

The data described in the WARNINGS AND PRECAUTIONS section reflect exposure to STIVARGA in more than 4800 patients who were enrolled in four randomized, placebo-controlled trials (n=1142), an expanded access program (CONSIGN, n=2864), or single arm clinical trials (single agent or in combination with other agents). There were 4518 patients who received STIVARGA as a single agent; the distribution of underlying malignancies was 80% CRC, 4% GIST, 10% HCC, 6% other solid tumors; and 74% were White, 11% Asian, and 15% race not known. Among these 4518 patients, 83% received STIVARGA for at least 21 days and 20% received STIVARGA for 6 months or longer.

In randomized placebo-controlled trials (CORRECT, GRID, RESORCE and CONCUR), the most frequently observed adverse drug reactions (≥20%) in patients receiving STIVARGA are pain (including gastrointestinal and abdominal pain), HFSR, asthenia/fatigue, diarrhea, decreased appetite/food intake, hypertension, infection, dysphonia, hyperbilirubinemia, fever, mucositis, weight loss, rash, and nausea.

Colorectal Cancer

The safety data described below, except where noted, are derived from a randomized (2:1), double-blind, placebo-controlled trial (CORRECT) in which 500 patients (median age 61 years; 61% men) with previously-treated metastatic colorectal cancer (CRC) received STIVARGA as a single agent at the dose of 160 mg daily for the first 3 weeks of each 4 week treatment cycle and 253 patients (median age 61 years; 60% men) received placebo. The median duration of therapy was 1.7 months (range 2 days, 10.8 months) for patients receiving STIVARGA. Due to adverse reactions, 61% of the patients receiving STIVARGA required a dose interruption and 38% of the patients had their dose reduced. Adverse reactions that resulted in treatment discontinuation occurred in 8.2% of STIVARGA-treated patients compared to 1.2% of patients who received placebo. Hand-foot skin reaction (HFSR) and rash were the most common reasons for permanent discontinuation of STIVARGA.

Table 1 provides the incidence of adverse reactions (≥10%) in patients in CORRECT.

Table 1: Adverse drug reactions reported in ≥10% of patients treated with STIVARGA in CORRECT and reported more commonly than in patients receiving placeboa
Adverse Reactions | STIVARGA (N=500) |  | Placebo (N=253)
Adverse Reactions | Grade |  | Grade
Adverse Reactions | All % | ≥ 3 % | All % | ≥ 3 %
General disorders and administration site conditions; Asthenia/fatigue; Pain; Fever | 64; 59; 28 | 15; 9; 2 | 46; 48; 15 | 9; 7; 0
Metabolism and nutrition disorders; Decreased appetite and food intake | 47 | 5 | 28 | 4
Skin and subcutaneous tissue disorders; HFSR/PPES; Rash b | 45; 26 | 17; 6 | 7; 4 | 0; <1
Gastrointestinal disorders; Diarrhea; Mucositis | 43; 33 | 8; 4 | 17; 5 | 2; 0
Investigations; Weight loss | 32 | <1 | 10 | 0
Infections and infestations; Infection c | 31 | 9 | 17 | 6
Vascular disorders; Hypertension; Hemorrhage c | 30; 21 | 8; 2 | 8; 8 | <1; <1
Respiratory, thoracic and mediastinal disorders; Dysphonia | 30 | 0 | 6 | 0
Nervous system disorders; Headache | 10 | <1 | 7 | 0

a Adverse reactions graded according to National Cancer Institute Common Toxicity for Adverse Events version 3.0 (NCI CTCAE v3.0).
b The term rash represents reports of events of drug eruption, rash, erythematous rash, generalized rash, macular rash, maculo-papular rash, papular rash, and pruritic rash.

c Fatal outcomes observed.

Table 2 provides laboratory abnormalities observed in CORRECT.

Table 2: Laboratory test abnormalities reported in CORRECT
Laboratory Parameter | STIVARGA (N=500 a) |  |  | Placebo (N=253 a)
Laboratory Parameter | Grade b |  |  | Grade b
Laboratory Parameter | All % | 3 % | 4 % | All % | 3 % | 4 %
Blood and lymphatic system disorders
Anemia | 79 | 5 | 1 | 66 | 3 | 0
Thrombocytopenia | 41 | 2 | <1 | 17 | <1 | 0
Neutropenia | 3 | 1 | 0 | 0 | 0 | 0
Lymphopenia | 54 | 9 | 0 | 35 | 4 | <1
Metabolism and nutrition disorders
Hypocalcemia | 59 | 1 | <1 | 18 | 1 | 0
Hypokalemia | 26 | 4 | 0 | 8 | <1 | 0
Hyponatremia | 30 | 7 | 1 | 22 | 4 | 0
Hypophosphatemia | 57 | 31 | 1 | 11 | 4 | 0
Hepatobiliary disorders
Hyperbilirubinemia | 45 | 10 | 3 | 17 | 5 | 3
Increased AST | 65 | 5 | 1 | 46 | 4 | 1
Increased ALT | 45 | 5 | 1 | 30 | 3 | <1
Renal and urinary disorders
Proteinuriac | 84 | 2 | 0 | 61 | 1 | 0
Investigations
Increased INRd | 24 | 4 | N/A | 17 | 2 | N/A
Increased Lipase | 46 | 9 | 2 | 19 | 3 | 2
Increased Amylase | 26 | 2 | <1 | 17 | 2 | <1

a % based on number of patients with post-baseline samples which may be less than 500 (regorafenib) or 253 (placebo).

b NCI CTCAE v3.0.

c Based on urine protein-creatinine ratio data.

d International normalized ratio: No Grade 4 denoted in NCI CTCAE, v3.0.

Gastrointestinal Stromal Tumors

The safety data described below are derived from a randomized (2:1), double-blind, placebo-controlled trial (GRID) in which 132 patients (median age 60 years; 64% men) with previously-treated GIST received STIVARGA as a single agent at a dose of 160 mg daily for the first 3 weeks of each 4 week treatment cycle and 66 patients (median age 61 years; 64% men) received placebo. The median duration of therapy was 5.7 months (range 1 day, 11.7 months) for patients receiving STIVARGA. Dose interruptions for adverse events were required in 58% of patients receiving STIVARGA and 50% of patients had their dose reduced. Adverse reactions that resulted in treatment discontinuation were reported in 2.3% of STIVARGA-treated patients compared to 1.5% of patients who received placebo.

Table 3 provides the incidence of adverse reactions (≥10%) in patients in GRID.

Table 3: Adverse reactions reported in ≥10% patients treated with STIVARGA in GRID and reported more commonly than in patients receiving placeboa
Adverse Reactions | STIVARGA (N=132) |  | Placebo (N=66)
Adverse Reactions | Grade |  | Grade
Adverse Reactions | All % | ≥ 3 % | All % | ≥ 3 %
Skin and subcutaneous tissue disorders; HFSR/PPE; Rash b; Alopecia | 67; 30; 24 | 22; 7; 2 | 12; 3; 2 | 2; 0; 0
General disorders and administration site conditions; Asthenia/Fatigue; Fever | 52; 21 | 4; 0 | 39; 11 | 2; 2
Vascular disorders; Hypertension; Hemorrhage | 59; 11 | 28; 4 | 27; 3 | 5; 0
Gastrointestinal disorders; Pain; Diarrhea; Mucositis; Nausea; Vomiting | 60; 47; 40; 20; 17 | 8; 8; 2; 2; <1 | 55; 9; 8; 12; 8 | 14; 0; 2; 2; 0
Respiratory, thoracic and mediastinal disorders; Dysphonia | 39 | 0 | 9 | 0
Infections and infestations; Infection c | 32 | 5 | 5 | 0
Metabolism and nutrition disorders; Decreased appetite and food intake; Hypothyroidism d | 31; 18 | <1; 0 | 21; 6 | 3; 0
Nervous system disorders; Headache | 16 | 0 | 9 | 0
Investigations; Weight loss | 14 | 0 | 8 | 0
Musculoskeletal and connective tissue disorders; Muscle spasms | 14 | 0 | 3 | 0

a Adverse reactions graded according to NCI CTCAE v4.0.

b The term rash represents reports of events of rash, erythematous rash, macular rash, maculo-papular rash, papular rash and pruritic rash.
c Fatal outcomes observed.

d Hypothyroidism incidence based on subset of patients with normal TSH and no thyroid supplementation at baseline.

Table 4 provides laboratory abnormalities observed in GRID.

Table 4: Laboratory test abnormalities reported in GRID
Laboratory Parameter | STIVARGA (N=132 a) |  |  | Placebo (N=66 a)
Laboratory Parameter | Grade b |  |  | Grade b
Laboratory Parameter | All % | 3 % | 4 % | All % | 3 % | 4 %
Blood and lymphatic system disorders; Thrombocytopenia; Neutropenia; Lymphopenia | 13; 16; 30 | 1; 2; 8 | 0; 1; 0 | 2; 12; 24 | 0; 3; 3 | 2; 0; 0
Metabolism and nutrition disorders; Hypocalcemia; Hypokalemia; Hypophosphatemia | 17; 21; 55 | 2; 3; 20 | 0; 0; 2 | 5; 3; 3 | 0; 0; 2 | 0; 0; 0
Hepatobiliary disorders; Hyperbilirubinemia; Increased AST; Increased ALT | 33; 58; 39 | 3; 3; 4 | 1; 1; 1 | 12; 47; 39 | 2; 3; 2 | 0; 0; 0
Renal and urinary disorders; Proteinuria c | 59 | 3 | - d | 53 | 3 | - d
Investigations; Increased Lipase | 14 | 0 | 1 | 5 | 0 | 0

a Percent based on number of patients with post-baseline samples which may be less than 132 (regorafenib) or 66 (placebo).

b NCI CTCAE v4.0.

c Based on urine protein-creatinine ratio data.

d No Grade 4 denoted in NCI CTCAE v4.0.

Hepatocellular Carcinoma

The safety data described below are derived from a randomized (2:1), double-blind, placebo-controlled trial (RESORCE) in which patients with previously-treated HCC received either STIVARGA (n=374) 160 mg orally on days 1-21 of each 4 week treatment cycle or placebo (n=193). The median age was 63 years, 88% were men, 98% had Child-Pugh A cirrhosis, 66% had an ECOG performance status (PS) of 0 and 34% had PS of 1. The median duration of therapy was 3.5 months (range 1 day to 29.4 months) for patients receiving STIVARGA. Of the patients receiving STIVARGA, 33% were exposed to STIVARGA for greater than or equal to 6 months and 14% were exposed to STIVARGA for greater than or equal to 12 months. Dose interruptions for adverse events were required in 58.3% of patients receiving STIVARGA and 48% of patients had their dose reduced. The most common adverse reactions requiring dose modification (interruption or dose reduction) were HFSR/PPES (20.6%), blood bilirubin increase (5.9%), fatigue (5.1%) and diarrhea (5.3%). Adverse reactions that resulted in treatment discontinuation were reported in 10.4% of STIVARGA-treated patients compared to 3.6% of patients who received placebo; the most common adverse reactions requiring discontinuation of STIVARGA were HFSR/PPES (1.9%) and AST increased (1.6%).

Table 5 provides the incidence of adverse reactions (≥10%) in patients in RESORCE.

Table 5: Adverse reactions reported in ≥10% of patients treated with STIVARGA in RESORCE and reported more commonly than in patients receiving placeboa
Adverse Reactions | STIVARGA (N=374) |  | Placebo (N=193)
Adverse Reactions | Grade |  | Grade
Adverse Reactions | All % | ≥ 3 % | All % | ≥ 3 %
Skin and subcutaneous tissue disorders; HFSR/PPE | 51 | 12 | 7 | <1
General disorders and administration site conditions; Pain; Asthenia/Fatigue; Fever | 55; 42; 20 | 9; 10; 0 | 44; 33; 7 | 8; 5; 0
Vascular disorders; Hypertension; Hemorrhage b | 31; 18 | 15; 5 | 6; 16 | 5; 8
Gastrointestinal disorders; Diarrhea; Nausea; Vomiting; Mucositis | 41; 17; 13; 13 | 3; <1; <1; 1 | 15; 13; 7; 2 | 0; 0; <1; ≤1
Respiratory, thoracic and mediastinal disorders; Dysphonia | 18 | 0 | 2 | 0
Infections and infestations; Infection b | 31 | 8 | 18 | 6
Metabolism and nutrition disorders; Decreased appetite and food intake | 31 | 3 | 15 | 2
Investigations; Weight loss | 13 | 2 | 4 | 0
Musculoskeletal and connective tissue disorders; Muscle spasms | 10 | 0 | 2 | 0

a Adverse reactions graded according to NCI CTCAE v4.0.

b Fatal outcomes observed.

Other clinically significant adverse reactions observed in less than 10% of STIVARGA-treated patients were: alopecia (7%), hypothyroidism (6.4%), pancreatitis (1.6%), exfoliative rash (1.3%), tremor (1.3%), erythema multiforme (0.8%), myocardial ischemia (0.8%), gastrointestinal fistula (0.3%), and myocardial infarction (0.3%).

Table 6 provides laboratory abnormalities observed in RESORCE.

Table 6: Laboratory test abnormalities reported in RESORCE
Laboratory Parameter | STIVARGA (N=374 a) |  |  | Placebo (N=193 a)
Laboratory Parameter | Grade b |  |  | Grade b
Laboratory Parameter | All % | 3 % | 4 % | All % | 3 % | 4 %
Blood and lymphatic system disorders; Thrombocytopenia; Neutropenia; Lymphopenia | 63; 14; 68 | 5; 3; 16 | <1; 0; 2 | 50; 15; 59 | 0; <1; 11 | 0; <1; <1
Metabolism and nutrition disorders; Hypocalcemia; Hypokalemia; Hypophosphatemia | 23; 31; 70 | <1; 4; 32 | 0; <1; 2 | 10; 9; 31 | 0; 2; 7 | 0; 0; 0
Hepatobiliary disorders; Hyperbilirubinemia; Increased AST; Increased ALT | 78; 93; 70 | 13; 16; 6 | 3; 2; <1 | 55; 84; 59 | 11; 17; 5 | 5; 3; 0
Renal and urinary disorders; Proteinuria c | 51 | 17 | - d | 37 | 3 | - d
Investigations; Increased INR; Increased Lipase; Increased Amylase | 44; 41; 23 | <1; 11; 3 | - d; 3; <1 | 35; 27; 19 | 2; 8; 2 | - d; 1; <1

a Percent based on number of patients with post-baseline samples which may be less than 374 (regorafenib) or 193 (placebo).

b NCI CTCAE v4.0.

c Based on dipstick data.

d No Grade 4 denoted in NCI CTCAE v4.0.

6.2 Postmarketing Experience

The following adverse reaction has been identified during postapproval use of STIVARGA. Because these reactions are reported voluntarily from a population of uncertain size, it is not always possible to reliably estimate their frequency or establish a causal relationship to drug exposure:

- hypersensitivity reaction
- nephrotic syndrome
- cardiac failure
- arterial (including aortic) aneurysms, dissections, and rupture

7 DRUG INTERACTIONS

7.1 Effect of Strong CYP3A4 Inducers on Regorafenib

Co-administration of a strong CYP3A4 inducer with STIVARGA decreased the plasma concentrations of regorafenib, increased the plasma concentrations of the active metabolite M-5, and resulted in no change in the plasma concentrations of the active metabolite M-2 [see Clinical Pharmacology (12.3)], and may lead to decreased efficacy. Avoid concomitant use of STIVARGA with strong CYP3A4 inducers (e.g. rifampin, phenytoin, carbamazepine, phenobarbital, and St. John's Wort).

7.2 Effect of Strong CYP3A4 Inhibitors on Regorafenib

Co-administration of a strong CYP3A4 inhibitor with STIVARGA increased the plasma concentrations of regorafenib and decreased the plasma concentrations of the active metabolites M-2 and M-5 [see Clinical Pharmacology (12.3)], and may lead to increased toxicity. Avoid concomitant use of STIVARGA with strong CYP3A4 inhibitors (e.g. clarithromycin, grapefruit juice, itraconazole, ketoconazole, nefazodone, posaconazole, telithromycin, and voriconazole).

7.3 Effect of Regorafenib on Breast Cancer Resistance Protein (BCRP) Substrates

Co-administration of STIVARGA with a BCRP substrate increased the plasma concentrations of the BCRP substrate [see Clinical Pharmacology (12.3)]. Monitor patients closely for signs and symptoms of exposure related toxicity to the BCRP substrate (e.g. methotrexate, fluvastatin, atorvastatin). Consult the concomitant BCRP substrate product information when considering administration of such products together with STIVARGA.

8 USE IN SPECIFIC POPULATIONS

8.1 Pregnancy

Risk Summary

Based on animal studies and its mechanism of action, STIVARGA can cause fetal harm when administered to a pregnant woman. There are no available data on STIVARGA use in pregnant women. Administration of regorafenib was embryolethal and teratogenic in rats and rabbits at exposures lower than human exposures at the recommended dose, with increased incidences of cardiovascular, genitourinary, and skeletal malformations [see Data]. Advise pregnant women of the potential hazard to a fetus.

The estimated background risk of major birth defects and miscarriage for the indicated population is unknown. In the U.S. general population, the estimated background risk of major birth defects and miscarriage in clinically recognized pregnancies is 2 to 4 % and 15 to 20%, respectively.

Data

Animal Data

In embryo-fetal development studies, a total loss of pregnancy (100% resorption of litter) was observed in rats at doses as low as 1 mg/kg (approximately 6% of the recommended human dose, based on body surface area) and in rabbits at doses as low as 1.6 mg/kg (approximately 25% of the human exposure at the clinically recommended dose measured by AUC).

In a single dose distribution study in pregnant rats, there was increased penetration of regorafenib across the blood-brain barrier in fetuses compared to dams. Daily administration of regorafenib to pregnant rats during organogenesis resulted in fetal findings of delayed ossification at doses > 0.8 mg/kg (approximately 5% of the recommended human dose based on body surface area) and dose-dependent increases in skeletal malformations including cleft palate and enlarged fontanelle at doses ≥ 1 mg/kg (approximately 10% of the clinical exposure based on AUC). At doses ≥ 1.6 mg/kg (approximately 11% of the recommended human dose based on body surface area), there were dose-dependent increases in the incidence of cardiovascular malformations, external abnormalities, diaphragmatic hernia, and dilation of the renal pelvis.

In pregnant rabbits administered regorafenib daily during organogenesis, there were findings of ventricular septal defects evident at the lowest tested dose of 0.4 mg/kg (approximately 7% of the AUC in patients at the recommended dose). At doses of ≥ 0.8 mg/kg (approximately 15% of the human exposure at the recommended human dose based on AUC), administration of regorafenib resulted in dose-dependent increases in the incidence of additional cardiovascular malformations and skeletal anomalies, as well as significant adverse effects on the urinary system including missing kidney/ureter; small, deformed and malpositioned kidney; and hydronephrosis. The proportion of viable fetuses that were male decreased with increasing dose in two rabbit embryo-fetal toxicity studies.

8.2 Lactation

Risk Summary

There are no data on the presence of regorafenib or its metabolites in human milk, the effects of regorafenib on the breastfed infant, or on milk production. In rats, regorafenib and its metabolites are excreted in milk. Because of the potential for serious adverse reactions in breastfed infants from STIVARGA, do not breastfeed during treatment with STIVARGA and for 2 weeks after the final dose.

8.3 Females and Males of Reproductive Potential

Contraception

Females

Use effective contraception during treatment and for 2 months after completion of therapy.

Males

Advise male patients with female partners of reproductive potential to use effective contraception during treatment and for 2 months following the final dose of STIVARGA [see Nonclinical Toxicology (13.1)].

Infertility

There are no data on the effect of STIVARGA on human fertility. Results from animal studies indicate that regorafenib can impair male and female fertility [see Nonclinical Toxicology (13.1)].

8.4 Pediatric Use

The safety and efficacy of STIVARGA in pediatric patients less than 18 years of age have not been established.

Animal Data

In 28-day repeat-dose studies in rats there were dose-dependent findings of dentin alteration and angiectasis. These findings occurred at regorafenib doses as low as 4 mg/kg (approximately 25% of the AUC in humans at the recommended dose). In 13-week repeat-dose studies in dogs there were similar findings of dentin alteration at doses as low as 20 mg/kg (approximately 43% of the AUC in humans at the recommended dose). Administration of regorafenib in these animals also led to persistent growth and thickening of the femoral epiphyseal growth plate.

8.5 Geriatric Use

Of the 1142 STIVARGA-treated patients enrolled in randomized, placebo-controlled trials, 40% were 65 years of age and over, while 10% were 75 and over. No overall differences in efficacy were observed between these patients and younger patients. There was an increased incidence of Grade 3 hypertension (18% versus 9%) in the placebo-controlled trials among STIVARGA-treated patients 65 years of age and older as compared to younger patients. In addition, one Grade 4 hypertension event has been reported in the 65 years and older age group and none in the younger age group.

8.6 Hepatic Impairment

No dose adjustment is recommended in patients with mild (total bilirubin ≤ULN and AST >ULN, or total bilirubin >ULN to ≤1.5 times ULN) or moderate (total bilirubin >1.5 to ≤3 times ULN and any AST) hepatic impairment, [see Clinical Pharmacology (12.3)]. Closely monitor patients with hepatic impairment for adverse reactions [see Warnings and Precautions (5.1)].

STIVARGA is not recommended for use in patients with severe hepatic impairment (total bilirubin >3x ULN) as STIVARGA has not been studied in this population.

8.7 Renal Impairment

No dose adjustment is recommended for patients with renal impairment. The pharmacokinetics of regorafenib have not been studied in patients who are on dialysis and there is no recommended dose for this patient population [see Clinical Pharmacology (12.3)].

8.8 Race

Based on pooled data from three placebo-controlled trials (CORRECT, GRID and CONCUR), a higher incidence of HFSR and liver function test abnormalities occurred in Asian patients treated with STIVARGA as compared with Whites [see Warnings and Precautions (5.1, 5.5)]. No starting dose adjustment is necessary based on race.

10 OVERDOSAGE

The highest dose of STIVARGA studied clinically is 220 mg per day. The most frequently observed adverse drug reactions at this dose were dermatological events, dysphonia, diarrhea, mucosal inflammation, dry mouth, decreased appetite, hypertension, and fatigue. There is no known antidote for STIVARGA overdose. In the event of suspected overdose, interrupt STIVARGA, institute supportive care, and observe until clinical stabilization.

11 DESCRIPTION

STIVARGA (regorafenib) is a multikinase inhibitor with the chemical name 4-[4-({[4-chloro-3-(trifluoromethyl) phenyl] carbamoyl} amino)-3-fluorophenoxy]-N-methylpyridine-2-carboxamide monohydrate. Regorafenib has the following structural formula:

Regorafenib is a monohydrate and it has a molecular formula C21H15ClF4N4O3 • H2O and a molecular weight of 500.83. Regorafenib is practically insoluble in water, slightly soluble in acetonitrile, methanol, ethanol, and ethyl acetate and sparingly soluble in acetone.

STIVARGA tablets for oral administration are formulated as light pink, oval-shaped tablets debossed with "BAYER" on one side and "40" on the other. Each tablet contains 40 mg of regorafenib in the anhydrous state, which corresponds to 41.49 mg of regorafenib monohydrate, and the following inactive ingredients: cellulose microcrystalline, croscarmellose sodium, magnesium stearate, povidone, and colloidal silicon dioxide. The film-coating contains the following inactive ingredients: ferric oxide red, ferric oxide yellow, lecithin (soy), polyethylene glycol 3350, polyvinyl alcohol, talc, and titanium dioxide.

12 CLINICAL PHARMACOLOGY

12.1 Mechanism of Action

Regorafenib is a small molecule inhibitor of multiple membrane-bound and intracellular kinases involved in normal cellular functions and in pathologic processes such as oncogenesis, tumor angiogenesis, metastasis and tumor immunity. In in vitro biochemical or cellular assays, regorafenib or its major human active metabolites M-2 and M-5 inhibited the activity of RET, VEGFR1, VEGFR2, VEGFR3, KIT, PDGFR-alpha, PDGFR-beta, FGFR1, FGFR2, TIE2, DDR2, TrkA, Eph2A, RAF-1, BRAF, BRAF V600E, SAPK2, PTK5, Abl and CSF1R at concentrations of regorafenib that have been achieved clinically. In in vivo models, regorafenib demonstrated anti-angiogenic activity in a rat tumor model and inhibition of tumor growth in several mouse xenograft models including some for human colorectal carcinoma, gastrointestinal stromal and hepatocellular carcinoma. Regorafenib also demonstrated anti-metastatic activity in a mouse xenograft model and two mouse orthotopic models of human colorectal carcinoma.

12.2 Pharmacodynamics

Cardiac Electrophysiology

The effect of multiple doses of STIVARGA (160 mg once daily for 21 days) on the QTc interval was evaluated in an open-label, single-arm study in 25 patients with advanced solid tumors. No large changes in the mean QTc interval (i.e., > 20 msec) were detected in the study.

12.3 Pharmacokinetics

Absorption

Following a single 160 mg dose of STIVARGA in patients with advanced solid tumors, regorafenib reaches a geometric mean peak plasma level (Cmax) of 2.5 µg/mL at a median time of 4 hours and a geometric mean area under the plasma concentration vs. time curve (AUC) of 70.4 µg*h/mL. The AUC of regorafenib at steady-state increases less than dose proportionally at doses greater than 60 mg. At steady-state, regorafenib reaches a geometric mean Cmax of 3.9 µg/mL and a geometric mean AUC of 58.3 µg*h/mL. The coefficient of variation of AUC and Cmax is between 35% and 44%.

The mean relative bioavailability of tablets compared to an oral solution is 69% to 83%.

In a food-effect study, 24 healthy men received a single 160 mg dose of STIVARGA on three separate occasions: under a fasted state, with a high-fat meal and with a low-fat meal. A high-fat meal (945 calories and 54.6 g fat) increased the mean AUC of regorafenib by 48% and decreased the mean AUC of the M-2 and M-5 metabolites by 20% and 51%, respectively, as compared to the fasted state. A low-fat meal (319 calories and 8.2 g fat) increased the mean AUC of regorafenib, M-2 and M-5 by 36%, 40% and 23%, respectively as compared to fasted conditions. STIVARGA was administered with a low-fat meal in the CORRECT and GRID studies [see Dosage and Administration (2.1), Clinical Studies (14)].

Distribution

Regorafenib undergoes enterohepatic circulation with multiple plasma concentration peaks observed across the 24-hour dosing interval. Regorafenib is highly bound (99.5%) to human plasma proteins.

Elimination

Following a single 160 mg oral dose of STIVARGA, the geometric mean (minimum to maximum) elimination half-lives for regorafenib and the M-2 metabolite in plasma are 28 hours (14 to 58 hours) and 25 hours (14 to 32 hours), respectively. M-5 has a longer mean (minimum to maximum) elimination half-life of 51 hours (32 to 70 hours).

Metabolism

Regorafenib is metabolized by CYP3A4 and UGT1A9. The main circulating metabolites of regorafenib measured at steady-state in human plasma are M-2 (N-oxide) and M-5 (N-oxide and N-desmethyl). Both metabolites have similar in vitro pharmacological activity and steady-state concentrations as regorafenib. M-2 and M-5 are highly protein bound (99.8% and 99.95%, respectively).

Excretion

Approximately 71% of a radiolabeled dose was excreted in feces (47% as parent compound, 24% as metabolites) and 19% of the dose was excreted in urine (17% as glucuronides) within 12 days after administration of a radiolabeled oral solution at a dose of 120 mg.

Specific Populations

Age, sex, race and weight had no clinically meaningful effect on the pharmacokinetics of regorafenib.

Hepatic Impairment

Based on a population pharmacokinetic analysis, no clinically important differences in the mean total exposure of regorafenib, including M-2 and M-5, were noted amongst patients with normal liver function (total bilirubin and AST ≤ ULN, n=744), mild hepatic impairment (total bilirubin ≤ ULN and AST >ULN or total bilirubin >ULN to ≤1.5x ULN, n=437), and moderate hepatic impairment (total bilirubin >1.5x to ≤3x ULN and any AST, n=36). The pooled analysis included 391 patients with HCC of whom 116, 249, and 26 were categorized as having normal liver function, mild, and moderate hepatic impairment, respectively. The pharmacokinetics of regorafenib were not evaluated in patients with severe hepatic impairment (total bilirubin >3x ULN).

Renal Impairment

The pharmacokinetics of regorafenib, M-2, and M-5 was evaluated in 6 patients with severe renal impairment (CLcr 15-29 mL/min) and 18 patients with normal/mild renal function (CLcr ≥60 mL/min) following the administration of STIVARGA at a dose of 160 mg daily for 21 days. No differences in the mean steady-state exposure of regorafenib, M-2, or M-5 were observed in patients with severe renal impairment compared to patients with normal renal function. The pharmacokinetics of regorafenib has not been studied in patients with end-stage renal disease on dialysis.

Drug Interaction Studies

Effect of Regorafenib on Cytochrome P450 Substrates: In vitro studies suggested that regorafenib is an inhibitor of CYP2C8, CYP2C9, CYP2B6, CYP3A4 and CYP2C19; M-2 is an inhibitor of CYP2C9, CYP2C8, CYP3A4 and CYP2D6, and M-5 is an inhibitor of CYP2C8. In vitro studies suggested that regorafenib is not an inducer of CYP1A2, CYP2B6, CYP2C19, and CYP3A4 enzyme activity.

Patients with advanced solid tumors received single oral doses of CYP substrates, 2 mg of midazolam (CYP3A4), 40 mg of omeprazole (CYP2C19) and 10 mg of warfarin (CYP2C9) or 4 mg of rosiglitazone (CYP2C8) one week before and two weeks after STIVARGA at a dose of 160 mg once daily. No clinically meaningful effect was observed in the mean AUC of rosiglitazone (N=12) or the mean omeprazole (N=11) plasma concentrations measured 6 hours after dosing or the mean AUC of midazolam (N=15). The mean AUC of warfarin (N=8) increased by 25% [see Warnings and Precautions (5.2)].

Effect of CYP3A4 Strong Inducers on Regorafenib: Twenty-two healthy men received a single 160 mg dose of STIVARGA alone and then 7 days after starting rifampin. Rifampin, a strong CYP3A4 inducer, was administered at a dose of 600 mg daily for 9 days. The mean AUC of regorafenib decreased by 50% and mean AUC of M-5 increased by 264%. No change in the mean AUC of M-2 was observed [see Drug Interactions (7.1)].

Effect of CYP3A4 Strong Inhibitors on Regorafenib: Eighteen healthy men received a single 160 mg dose of STIVARGA alone and then 5 days after starting ketoconazole. Ketoconazole, a strong CYP3A4 inhibitor, was administered at a dose of 400 mg daily for 18 days. The mean AUC of regorafenib increased by 33% and the mean AUC of M-2 and M-5 both decreased by 93% [see Drug Interactions (7.2)].

Effect of Neomycin on Regorafenib: Twenty-seven healthy men received a single 160 mg dose of STIVARGA and then 5 days after starting neomycin. Neomycin, a non-absorbable antibiotic, was administered at a dose of 1 gram three times daily for 5 days. No clinically meaningful effect on the mean AUC of regorafenib was observed; however, the mean AUC of M-2 decreased by 76% and the mean AUC of M-5 decreased by 86%. The decreased exposure of M-2 and M-5 may result in a decreased efficacy of STIVARGA. The effects of other antibiotics on the exposure of regorafenib and its active metabolites have not been studied.

Effect of Regorafenib on UGT1A1 Substrates: In vitro studies showed that regorafenib, M-2, and M-5 competitively inhibit UGT1A9 and UGT1A1 at therapeutically relevant concentrations. Eleven patients received irinotecan-containing combination chemotherapy with STIVARGA at a dose of 160 mg. The mean AUC of irinotecan increased by 28% and the mean AUC of SN-38 increased by 44% when irinotecan was administered 5 days after the last of 7 daily doses of STIVARGA.

Effect of Regorafenib on BCRP Substrates: Administration of regorafenib (160 mg for 14 days) prior to administration of a single dose of rosuvastatin (5 mg), a BCRP substrate, resulted in a 3.8-fold increase in mean exposure (AUC) of rosuvastatin and a 4.6-fold increase in Cmax [see Drug Interactions (7.3)].

13 NONCLINICAL TOXICOLOGY

13.1 Carcinogenesis, Mutagenesis, Impairment of Fertility

Studies examining the carcinogenic potential of regorafenib have not been conducted. Regorafenib itself did not demonstrate genotoxicity in in vitro or in vivo assays; however, a major human active metabolite of regorafenib, (M-2), was positive for clastogenicity, causing chromosome aberration in Chinese hamster V79 cells.

Dedicated studies to examine the effects of regorafenib on fertility have not been conducted; however, there were histological findings of tubular atrophy and degeneration in the testes, atrophy in the seminal vesicle, and cellular debris and oligospermia in the epididymides in male rats at doses similar to those in human at the clinical recommended dose based on AUC. In female rats, there were increased findings of necrotic corpora lutea in the ovaries at the same exposures. There were similar findings in dogs of both sexes in repeat dose studies at exposures approximately 83% of the human exposure at the recommended human dose based on AUC. These findings suggest that regorafenib may adversely affect fertility in humans.

13.2 Animal Toxicology and/or Pharmacology

In a chronic 26-week repeat dose study in rats there was a dose-dependent increase in the finding of thickening of the atrioventricular valve. At a dose that resulted in an exposure of approximately 12% of the human exposure at the recommended dose, this finding was present in half of the examined animals.

14 CLINICAL STUDIES

14.1 Colorectal Cancer

The clinical efficacy and safety of STIVARGA were evaluated in an international, multicenter, randomized (2:1), double-blind, placebo-controlled trial [Study "Patients with metastatic COloRectal cancer treated with REgorafenib or plaCebo after failure of standard Therapy" (CORRECT); NCT 01103323)] in 760 patients with previously-treated metastatic colorectal cancer. The major efficacy outcome measure was overall survival (OS); additional efficacy outcome measures included progression-free survival (PFS) and overall tumor response rate.

Patients were randomized to receive 160 mg regorafenib orally once daily (N=505) plus best supportive care (BSC) or placebo (N=255) plus BSC for the first 21 days of each 28-day cycle. STIVARGA was administered with a low-fat breakfast that contains less than 30% fat [see Dosage and Administration (2.1), Clinical Pharmacology (12.3)]. Treatment continued until disease progression or unacceptable toxicity.

Baseline demographics were: median age 61 years, 61% men, 78% White, and all patients had an ECOG performance status of 0 or 1. The primary sites of disease were colon (65%), rectum (29%), or both (6%). History of KRAS evaluation was reported for 729 (96%) patients; 430 (59%) of these patients were reported to have KRAS mutation. The median number of prior lines of therapy for metastatic disease was 3. All patients received prior treatment with fluoropyrimidine-, oxaliplatin-, and irinotecan-based chemotherapy, and with bevacizumab. All but one patient with KRAS mutation-negative tumors received panitumumab or cetuximab.

The addition of STIVARGA to BSC resulted in a statistically significant improvement in survival compared to placebo plus BSC (see Table 7 and Figure 1).

Table 7: Efficacy Results from CORRECT
 | STIVARGA (N=505) | Placebo (N=255)
Overall Survival
Number of Deaths (%) | 275 (55%) | 157 (62%)
Median Overall Survival (months) | 6.4 | 5.0
95% CI a | (5.8, 7.3) | (4.4, 5.8)
Hazard Ratio (HR) (95% CI) | 0.77 (0.64, 0.94)
Stratified log-rank test p-value b, c | 0.0102
Progression-Free Survival
Number of Deaths or Progressions (%) | 417 (83%) | 231 (91%)
Median Progression-Free Survival (months) | 2.0 | 1.7
95% CI | (1.9, 2.3) | (1.7, 1.8)
HR (95% CI) | 0.49 (0.42, 0.58)
Stratified log-rank test p-value c | <0.0001
Overall Response Rate
Overall Response, N (%) | 5 (1%) | 1 (0.4%)
95% CI | 0.3%, 2.3% | 0%, 2.2%

a CI=confidence interval.
b Stratified by geographic region and time from diagnosis of metastatic disease.
c Crossed the O'Brien-Fleming boundary (two-sided p-value < 0.018) at second interim analysis.

Figure 1: Kaplan-Meier Curves of Overall Survival

14.2 Gastrointestinal Stromal Tumors

The efficacy and safety of STIVARGA were evaluated in an international, multicenter, randomized (2:1), double-blind, placebo-controlled trial [Study "GIST Regorafenib In progressive Disease" (GRID); NCT 01271712] in patients with unresectable, locally advanced or metastatic gastrointestinal stromal tumor (GIST), who had been previously treated with imatinib mesylate and sunitinib malate. Randomization was stratified by line of therapy (third vs. four or more) and geographic region (Asia vs. rest of the world).

The major efficacy outcome measure of GRID was progression-free survival (PFS) based on disease assessment by independent radiological review using modified RECIST 1.1 criteria, in which lymph nodes and bone lesions were not target lesions and progressively growing new tumor nodule within a pre-existing tumor mass was progression. The key secondary outcome measure was overall survival.

Patients were randomized to receive 160 mg regorafenib orally once daily (N=133) plus best supportive care (BSC) or placebo (N=66) plus BSC for the first 21 days of each 28-day cycle. Treatment continued until disease progression or unacceptable toxicity. In GRID, the median age of patients was 60 years, 64% were men, 68% were White, and all patients had baseline ECOG performance status of 0 (55%) or 1 (45%). At the time of disease progression as assessed by central review, the study blind was broken and all patients were offered the opportunity to take STIVARGA at the investigator's discretion.

A statistically significant improvement in PFS was demonstrated among patients treated with STIVARGA compared to placebo (see Table 8 and Figure 2).

There was no statistically significant difference in overall survival at the final OS analysis, conducted at 162 OS events (Table 8). Cross-over to open label STIVARGA occurred in 58 (88%) placebo-treated patients after disease progression.

Table 8: Efficacy Results for GRID
 | STIVARGA; (N=133) | Placebo; (N=66)
Progression-Free Survival
Number of Deaths or Progressions (%) | 82 (62%) | 63 (96%)
Median PFS in months (95% CI) | 4.8 (3.9, 5.7) | 0.9 (0.9, 1.1)
HR (95% CI) | 0.27 (0.19, 0.39)
p-value a | <0.0001
Overall Survival
Number of Deaths (%) | 109 (82%) | 53 (80.3%)
Median OS in Months (95% CI) | 17.4 (14.9, 20.2) | 17.4 (12.3, 21.0)
HR (95% CI) | 0.91 (0.65, 1.27)
p-value a | 0.5716

a 2-sided p-value by log-rank test stratified by line of treatment and geographical region.

Figure 2: Kaplan-Meier Curves of Progression-Free Survival for GRID

14.3 Hepatocellular Carcinoma (HCC)

The clinical efficacy and safety of STIVARGA were evaluated in an international, multicenter, randomized (2:1), double-blind, placebo-controlled trial [Study "REgorafenib after SORafenib in patients with hepatoCEllular carcinoma" (RESORCE); NCT 01774344]. The study enrolled adults with Child-Pugh A and Barcelona Clinic Liver Cancer Stage Category B or C hepatocellular carcinoma, with documented disease progression following sorafenib. The median duration of previous sorafenib treatment was 7.8 months; patients who permanently discontinued sorafenib due to toxicity or were unable to tolerate sorafenib doses of 400 mg once daily were ineligible.

Patients were randomized to receive 160 mg regorafenib orally once daily plus best supportive care (BSC) or matching placebo plus BSC for the first 21 days of each 28-day cycle until disease progression or unacceptable toxicity. Randomization was stratified by geographical region (Asia vs rest of world), ECOG performance status (0 vs 1), alpha-fetoprotein levels (<400 ng/mL vs ≥400 ng/mL), extrahepatic disease (presence vs absence), and macrovascular invasion (presence vs absence). The major efficacy outcome measure was overall survival (OS). Additional outcome measures were progression-free survival (PFS), overall tumor response rate (ORR) and duration of response as assessed by investigators using RECIST 1.1 and using modified RECIST (mRECIST) for HCC. Patients continued therapy with STIVARGA until clinical or radiological disease progression or unacceptable toxicity.

The characteristics of the study population were a median age of 63 years (range 19 to 85 years); 88% male; 41% Asian, 36% White, and 21% not reported; 66% had ECOG performance status (PS) of 0 and 34% had ECOG PS of 1; 98% had Child-Pugh A and 2% had Child-Pugh B. Risk factors for underlying cirrhosis included hepatitis B (38%), alcohol use (25%), hepatitis C (21%), and non-alcoholic steato hepatitis (7%). Macroscopic vascular invasion or extra-hepatic tumor spread was present in 81% of patients. Barcelona Clinic Liver Cancer (BCLC) was stage C in 87% and stage B in 13% of patients. All patients received prior sorafenib and 61% received prior loco-regional transarterial embolization or chemoinfusion procedures.

Efficacy results are summarized in Table 9 and Figure 3 below.

Table 9: Efficacy Results from Study RESORCE
 | STIVARGA; n=379 | Placebo; n=194
Overall Survival
Number of Deaths (%) | 233 (62) | 140 (72)
Median OS in months (95% CIa) | 10.6 (9.1, 12.1) | 7.8 (6.3, 8.8)
Hazard Ratiob (95% CIa) | 0.63 (0.50, 0.79)
P-valuec | <0.0001
Progression-free Survival (mRECIST)
Number of Events (%) | 293 (77) | 181(93)
Progressive Disease | 274 (72) | 173 (89)
Death | 19 (5) | 8 (4)
Median PFS in months (95% CIa) | 3.1 (2.8, 4.2) | 1.5 (1.4, 1.6)
Hazard Ratiob (95% CIa) | 0.46 (0.37, 0.56)
P-valuec | <0.0001
Progression-free Survival (RECIST 1.1)
Number of Events (%) | 288 (76) | 184 (95)
Progressive Disease | 270 (71) | 175 (90)
Death | 18 (5) | 9 (5)
Median PFS in months (95% CIa) | 3.4 (2.9, 4.2) | 1.5 (1.4, 1.5)
Hazard Ratiob (95% CIa) | 0.43 (0.35, 0.52)
Overall Response (mRECIST)
Overall Response Rate | 11% | 4%
95% CIa | (8%, 14%) | (2%, 8%)
Complete Response | 0.5% | 0
Partial Response | 10% | 4%
Overall Response (RECIST 1.1)
Overall Response Rate | 7% | 3%
95% CIa | (4%, 10%) | (1%, 6%)
Complete Response | 0 | 0
Partial Response | 7% | 3%

a CI=confidence interval.
b Estimated with Cox proportional hazard model stratified by geographic region, ECOG performance status, Alpha-fetoprotein level, presence versus absence of extrahepatic disease, and presence versus absence of macrovascular invasion.
c Log rank test stratified by geographic region, ECOG performance status, Alpha-fetoprotein level, presence versus absence of extrahepatic disease, and presence versus absence of macrovascular invasion.

Figure 3: Kaplan-Meier Curve of Overall Survival from Study RESORCE

16 HOW SUPPLIED/STORAGE AND HANDLING

How Supplied

STIVARGA (regorafenib) is supplied as 40 mg tablets that are light pink, oval-shaped, film-coated tablets, debossed with 'BAYER' on one side and '40' on the other side in the following:

- Packages containing three bottles, with each bottle containing 28 tablets, for a total of 84 tablets per package
  (NDC 50419-171-03).
- Packages containing four bottles, with each bottle containing 21 tablets, for a total of 84 tablets per package
  (NDC 50419-171-06).

Storage and Handling

Store STIVARGA at 25°C (77°F); excursions are permitted from 15 to 30°C (59 to 86°F) [see USP Controlled Room Temperature].

Store tablets in the original bottle and do not remove the desiccant. Keep the bottle tightly closed after first opening.

Discard any unused tablets 7 weeks after opening the bottle. Dispose of unused tablets in accordance with local requirements.

17 PATIENT COUNSELING INFORMATION

Advise the patient to read the FDA-approved patient labeling (Patient Information).

Hepatotoxicity

Advise patients that they will need to undergo monitoring for liver damage and to report immediately any signs or symptoms of severe liver damage to their healthcare provider. Advise patients to contact their healthcare provider immediately if they experience a severe and/or persistent headache, visual disturbances, seizures, noticeable decrease in energy, drowsiness, trembling, confusion, memory loss or disorientation [see Warnings and Precautions (5.1), Use in Specific Populations (8.6)].

Infections

Advise patients to contact their healthcare provider if they experience signs and symptoms of infection [see Warnings and Precautions (5.2)].

Hemorrhage

Advise patients to contact their healthcare provider for unusual bleeding, bruising, or symptoms of bleeding, such as lightheadedness [see Warnings and Precautions (5.3)].

Gastrointestinal Perforation or Fistula

Advise patients to contact a healthcare provider immediately if they experience severe pains in their abdomen, persistent swelling of the abdomen, high fever, chills, nausea, vomiting, or dehydration [see Warnings and Precautions (5.4)].

Dermatologic Toxicity

Advise patients to contact their healthcare provider if they experience skin changes including HFSR, rash, pain, blisters, bleeding, or swelling [see Warnings and Precautions (5.5)].

Hypertension

Advise patients they will need to undergo blood pressure monitoring and to contact their healthcare provider if blood pressure is elevated or if symptoms from hypertension occur including severe headache, lightheadedness, or neurologic symptoms [see Warnings and Precautions (5.6)].

Cardiac Ischemia and Infarction

Advise patients to seek immediate emergency help if they experience chest pain, shortness of breath, feel dizzy, or feel like passing out [see Warnings and Precautions (5.7)].

Reversible Posterior leukoencephalopathy syndrome

Advise patients to contact their healthcare provider if they experience signs and symptoms of RPLS [see Warnings and Precautions (5.8)].

Risk of Impaired Wound Healing

Advise patients that STIVARGA may impair wound healing. Advise patients that temporary interruption of STIVARGA is recommended prior to any elective surgery [see Warnings and Precautions (5.9)].

Embryo-Fetal Toxicity

Advise patients that regorafenib can cause fetal harm. Advise a pregnant woman of the potential risk to a fetus [see Warnings and Precautions (5.10), Use in Specific Populations (8.1, 8.3)].

Females and Males of Reproductive Potential

- Advise women of reproductive potential of the need for effective contraception during STIVARGA treatment and for 2 months after completion of treatment. Instruct women of reproductive potential to immediately contact her healthcare provider if pregnancy is suspected or confirmed during or within 2 months of completing treatment with STIVARGA [see Warnings and Precautions (5.10) and Use in Specific Populations (8.1, 8.3)].
- Advise men of reproductive potential of the need for effective contraception during STIVARGA treatment and for 2 months after completion of treatment [see Use in Specific Populations (8.3)].

Lactation

Advise nursing mothers that it is not known whether regorafenib is present in breast milk and discuss whether to discontinue nursing or to discontinue regorafenib [see Use in Specific Populations (8.2)].

Administration

- Advise patients to swallow the STIVARGA tablet whole with water at the same time each day following a low-fat meal. Inform patients that the low-fat meal should contain less than 600 calories and less than 30% fat [see Dosage and Administration (2.1)].
- Advise patients to store medicine in the original container. Do not place medication in daily or weekly pill boxes. Discard any remaining tablets 7 weeks after opening the bottle. Tightly close bottle after each opening and keep the desiccant in the bottle [see How Supplied (16)].

Dosing Instructions

Advise patients to take STIVARGA after a low fat meal. Advise patients to take any missed dose on the same day, as soon as they remember, and that they must not take two doses on the same day to make up for a dose missed on the previous day [see Dose and Administration (2.1)].

Manufactured for:

Bayer HealthCare Pharmaceuticals Inc.
Whippany, NJ 07981 USA

Patient Information

STIVARGA (sti-VAR-gah)

(regorafenib)

tablets

What is the most important information I should know about STIVARGA?

STIVARGA can cause serious side effects, including:

- liver problems. STIVARGA can cause severe liver problems, including increased blood ammonia, which can sometimes lead to death. Your healthcare provider will do blood tests to check your liver function before you start taking STIVARGA and during your treatment with STIVARGA to check for liver problems. Tell your healthcare provider right away if you get any of these signs or symptoms of liver problems during treatment:

- yellowing of your skin or the white part of your eyes (jaundice)
- pain on the upper right side of your stomach area (abdomen)
- nausea or vomiting
- loss of appetite
- light-colored stools (bowel movements)
- dark "tea-colored" urine
- severe headache or headaches that persist

- vision changes
- seizures
- feeling more tired than usual
- drowsiness
- trembling
- confusion
- memory loss or disorientation

See "What are the possible side effects of STIVARGA?" for more information about side effects.

What is STIVARGA?

STIVARGA is a prescription medicine used to treat adults with:

- colon or rectal cancer that has spread to other parts of the body and for which they have received previous treatment with certain chemotherapy medicines
- a rare stomach, bowel, or esophagus cancer called GIST (gastrointestinal stromal tumors) that cannot be treated with surgery or that has spread to other parts of the body and for which they have received previous treatment with certain medicines
- a type of liver cancer called hepatocellular carcinoma (HCC) in people who have been previously treated with sorafenib

It is not known if STIVARGA is safe and effective in children less than 18 years of age.

Before taking STIVARGA, tell your healthcare provider about all of your medical conditions, including if you:

- have liver problems in addition to liver cancer
- have bleeding problems
- have high blood pressure
- have heart problems or chest pain
- plan to have surgery or have had a recent surgery. You should stop taking STIVARGA at least 2 weeks before planned surgery. See "What are the possible side effects of STIVARGA?"
- are pregnant or plan to become pregnant. STIVARGA can harm your unborn baby.
  - Females should use effective birth control during treatment with STIVARGA and for 2 months after your final dose of STIVARGA. Tell your healthcare provider right away if you become pregnant during treatment with STIVARGA or within 2 months after your final dose of STIVARGA.
  - Males with female partners who can become pregnant should use effective birth control during treatment with STIVARGA and for 2 months after your final dose of STIVARGA.
- are breastfeeding or plan to breastfeed. It is not known if STIVARGA passes into your breast milk. Do not breastfeed during treatment with STIVARGA and for 2 weeks after your final dose of STIVARGA.

Tell your healthcare provider about all the medicines you take, including prescription and over-the-counter medicines, vitamins and herbal supplements. STIVARGA may affect the way other medicines work, and other medicines may affect how STIVARGA works.

How should I take STIVARGA?

- Take STIVARGA exactly as your healthcare provider tells you.
- You will usually take STIVARGA 1 time a day for 21 days (3 weeks) and then stop for 7 days (1 week). This is 1 cycle of treatment. Repeat this cycle for as long as your healthcare provider tells you to.
- Swallow STIVARGA tablets whole with water following a low-fat meal.
- Take STIVARGA at the same time each day following a low-fat meal that contains less than 600 calories and less than 30% fat.
- If you miss a dose, take it as soon as you remember on that day. Do not take two doses on the same day to make up for a missed dose.
- If you take too much STIVARGA call your healthcare provider or go to the nearest emergency room right away.

What should I avoid while taking STIVARGA?

- Avoid drinking grapefruit juice and taking St. John's Wort during treatment with STIVARGA. These can affect the way STIVARGA works.

What are the possible side effects of STIVARGA?

STIVARGA can cause serious side effects including:

- See "What is the most important information I should know about STIVARGA?"
- infection. STIVARGA may lead to a higher risk of infections especially of the urinary tract, nose, throat and lung. STIVARGA may also lead to a higher risk of fungal infections of the mucous membrane, skin or the body. Tell your healthcare provider right away if you get:

- fever
- severe cough with or without an increase in mucus
  (sputum) production
- severe sore throat
- shortness of breath

- burning or pain when urinating
- unusual vaginal discharge or irritation
- redness, swelling or pain in any part of the body

- severe bleeding. STIVARGA can cause bleeding which can be serious and sometimes lead to death. Tell your healthcare provider if you have any signs of bleeding during treatment with STIVARGA including:

- vomiting blood or if your vomit looks like coffee-grounds
- pink or brown urine
- red or black (looks like tar) stools
- coughing up blood or blood clots
- menstrual bleeding that is heavier than normal

- unusual vaginal bleeding
- nose bleeds that happen often
- bruising
- lightheadedness

- a tear in your stomach or intestinal wall (bowel perforation). STIVARGA may cause a tear in your stomach or intestinal wall (bowel perforation) that can be serious and sometimes lead to death. Tell your healthcare provider right away if you get:

- severe pain in your stomach-area (abdomen)
- swelling of the abdomen
- fever
- chills

- nausea
- vomiting
- dehydration

- a skin problem called hand-foot skin reaction and severe skin rash. Hand-foot skin reactions are common and sometimes can be severe. Tell your healthcare provider right away if you get redness, pain, blisters, bleeding, or swelling on the palms of your hands or soles of your feet, or a severe rash.
- high blood pressure. Your blood pressure should be checked every week for the first 6 weeks of starting STIVARGA. Your blood pressure should be checked regularly and any high blood pressure should be treated during treatment with STIVARGA. Tell your healthcare provider if you have severe headaches, lightheadedness, or changes in your vision.
- decreased blood flow to the heart and heart attack. Get emergency help right away if you get symptoms such as chest pain, shortness of breath, feel dizzy or feel like passing out.
- a condition called Reversible Posterior Leukoencephalopathy Syndrome (RPLS). Call your healthcare provider right away if you get severe headaches, seizure, confusion, change in vision, or problems thinking.
- risk of wound healing problems. Wounds may not heal properly during STIVARGA treatment. Tell your healthcare provider if you plan to have any surgery before starting or during treatment with STIVARGA.
  - You should stop taking STIVARGA at least 2 weeks before planned surgery.
  - Your healthcare provider should tell you when you may start taking STIVARGA again after surgery.

The most common side effects of STIVARGA include:

- pain, including stomach-area (abdomen)
- tiredness, weakness, fatigue
- frequent or loose bowel movements (diarrhea)
- decreased appetite
- infection

- voice changes or hoarseness
- increase in certain liver function test
- fever
- swelling, pain and redness of the lining in your mouth, throat, stomach and bowel (mucositis)
- weight loss

Your healthcare provider may change your dose, temporarily stop, or permanently stop treatment with STIVARGA if you have certain side effects.

These are not all of the possible side effects of STIVARGA.

Call your doctor for medical advice about side effects. You may report side effects to FDA at 1-800-FDA-1088.

How do I store STIVARGA?

- Store STIVARGA tablets at room temperature between 68° F to 77° F (20° C to 25°C).
- Keep STIVARGA in the bottle that it comes in. Do not put STIVARGA tablets in a daily or weekly pill box.
- The STIVARGA bottle contains a desiccant to help keep your medicine dry. Keep the desiccant in the bottle.
- Keep the bottle of STIVARGA tightly closed.
- Safely throw away (discard) any unused STIVARGA tablets after 7 weeks of opening the bottle.

Keep STIVARGA and all medicines out of the reach of children.

General information about the safe and effective use of STIVARGA.

Medicines are sometimes prescribed for purposes other than those listed in a Patient Information leaflet. Do not use STIVARGA for a condition for which it was not prescribed. Do not give STIVARGA to other people even if they have the same symptoms you have. It may harm them. You can ask your healthcare provider or pharmacist for information about STIVARGA that is written for health professionals.

What are the ingredients in STIVARGA?

Active ingredient: regorafenib

Inactive ingredients: cellulose microcrystalline, croscarmellose sodium, magnesium stearate, povidone and colloidal silicon dioxide.

Film coat: ferric oxide red, ferric oxide yellow, lecithin (soy), polyethylene glycol 3350, polyvinyl alcohol, talc and titanium dioxide.

Manufactured for Bayer HealthCare Pharmaceuticals Inc., Whippany, NJ 07981 USA. © 2017 Bayer HealthCare Pharmaceuticals Inc.
For more information, go to www.STIVARGA-US.com or call 1-888-842-2937.

This Patient Information has been approved by the U.S. Food and Drug Administration.

Revised: 2/2026

PACKAGE/LABEL PRINCIPAL DISPLAY PANEL

NDC 50419-171-03

Rx Only
Stivarga
(regorafenib) tablets
40 mg

3 x 28 tablets
for oral administration